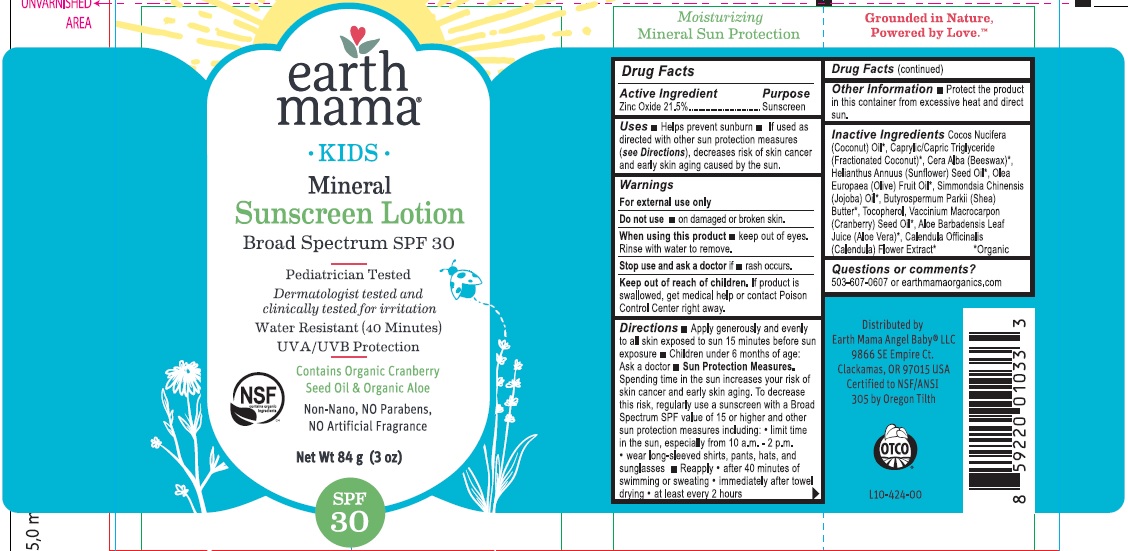 DRUG LABEL: SUNSCREEN
NDC: 62932-171 | Form: OINTMENT
Manufacturer: Private Label Select Ltd CO
Category: otc | Type: HUMAN OTC DRUG LABEL
Date: 20181108

ACTIVE INGREDIENTS: ZINC OXIDE 22 g/100 g
INACTIVE INGREDIENTS: CRANBERRY SEED OIL; COCONUT OIL; SUNFLOWER OIL; SHEA BUTTER; CALENDULA OFFICINALIS FLOWER; TOCOPHEROL; CAPRYLIC/CAPRIC/LAURIC TRIGLYCERIDE; YELLOW WAX; SIMMONDSIA CHINENSIS SEED WAX; OLEA EUROPAEA FRUIT VOLATILE OIL; ALOE VERA LEAF

earth mama Kids Mineral Sunscreen SPF30